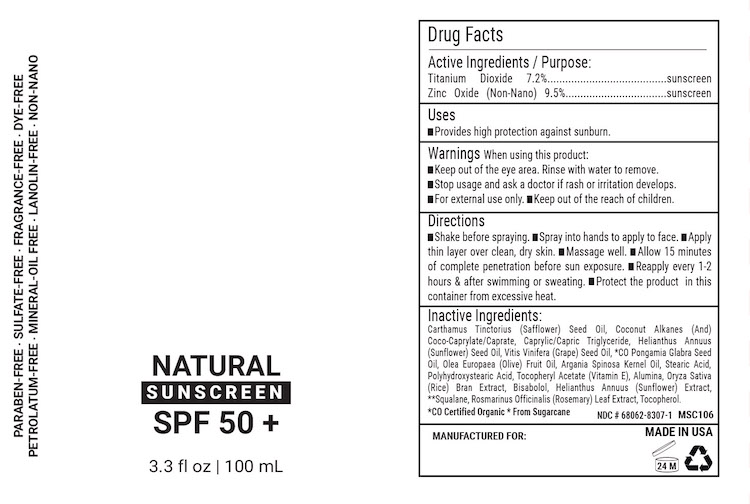 DRUG LABEL: Natural SPF 50
NDC: 68062-8307 | Form: LOTION
Manufacturer: Spa de Soleil
Category: otc | Type: HUMAN OTC DRUG LABEL
Date: 20260120

ACTIVE INGREDIENTS: TITANIUM DIOXIDE 780 mg/118 mL; ZINC OXIDE 900 mg/118 mL
INACTIVE INGREDIENTS: WATER; JOJOBA OIL; SHEA BUTTER; ETHYL MACADAMIATE; XANTHAN GUM; SQUALANE

Natural SPF 50

Active Ingredients

Titanium Dioxide 7.2%

Zinc Oxide 9.52%

Purpose

Sunscreen

Warnings

Warnings When using this product

- keep out of the eye area
- rinse with water to remove
- stop use and ask a doctor if rash or irritation develops
- for external use onlyl
- keep out of reach of children

Keep out of reach of children.

DOSAGE AND ADMINISTRATION

Directions: for sunscreen use
● apply generously 15 minutes before sun exposure
● apply to all skin exposed to the sun
● children under 6 months of age: Ask a doctor

INDICATIONS AND USAGE

Directions: for sunscreen use
● apply generously 15 minutes before sun exposure
● apply to all skin exposed to the sun
● children under 6 months of age: Ask a doctor

Inactive Ingredients

carthamus tinctorius (safflower) seed oil, coconut alkanes, coco caprylate/caprate, caprylic/capric triglyceride, stearic acid, alumina, polyhydroxystearic acid, helianthus annuus (sunflower) seed oil, pongamia glabra (karanja) seed oil, vitis vinifera (grape) see oil, olea europaea (olive) oil, argania spinosa (argan) oil, oryza sativa (rice) bran extract, rosarinus officnailis (rosemary) extract, tocopherol, argania spinosa kernel oil, tocopheryl acetate (vitamin E), bisabolol, squalane